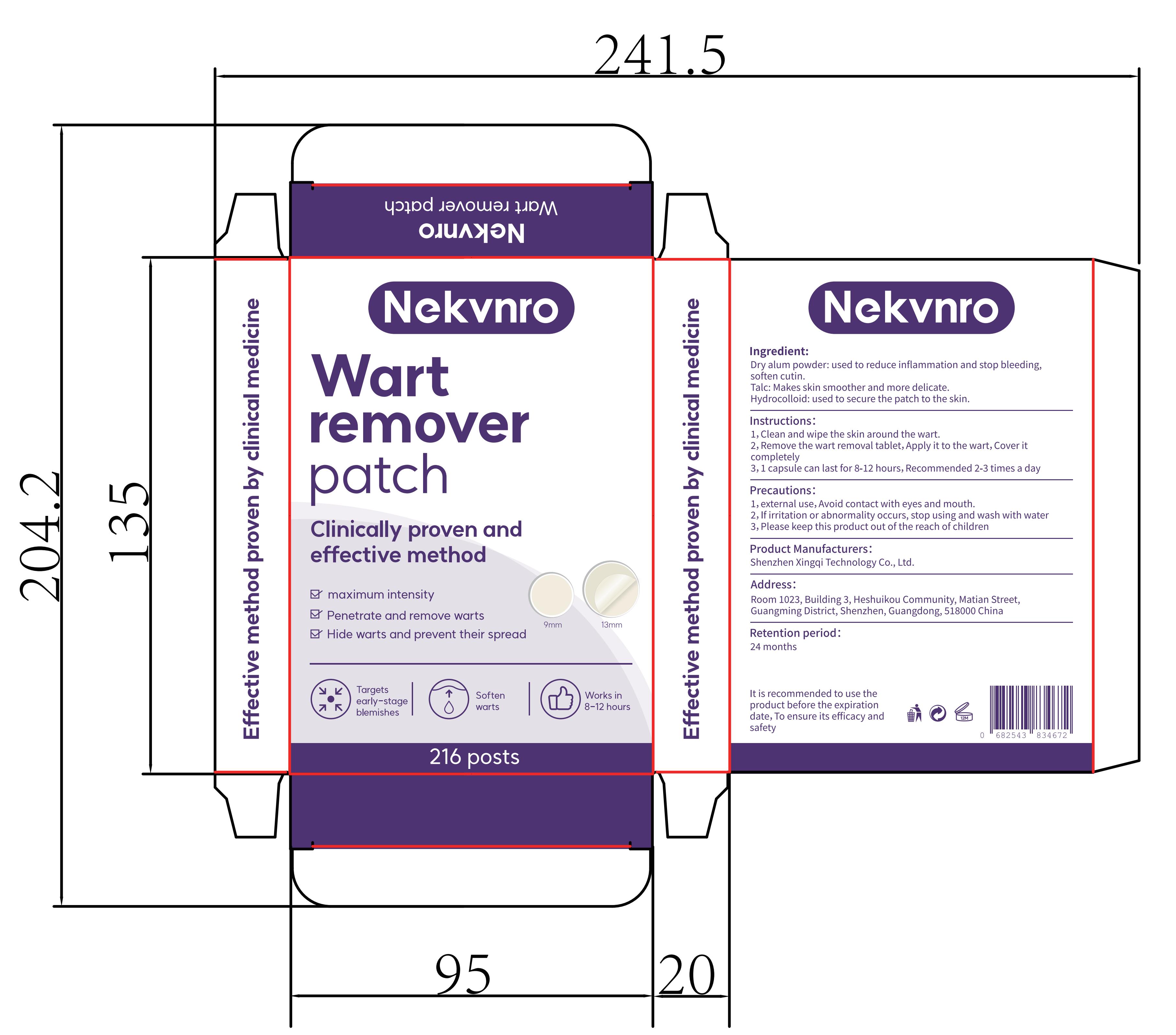 DRUG LABEL: Nekvnro Wart remover patch
NDC: 84613-052 | Form: PATCH
Manufacturer: Shenzhen Xingqi Technology Co., Ltd.
Category: otc | Type: HUMAN OTC DRUG LABEL
Date: 20240808

ACTIVE INGREDIENTS: TALC 1 g/100 g
INACTIVE INGREDIENTS: POTASSIUM ALUM 1 g/100 g; SODIUM ALGINATE

ACTIVE INGREDIENT

TALC 1%

PURPOSE

wart removal

USES

1, Clean and wipe the skin around the wart.
2, Remove the wart removal tablet, Apply it to the wart,Cover it completely
3, 1 capsule can last for 8-12hours,Recommended 2-3 times a day

warning

1, external use,Avoid contact with eyes and mouth.
2,If irritation or abnormality occurs, stop using and wash with water
3, Please keep this product out of the reach of children

Dosage and administration

For external use only.

Do not use

1, external use, Avoid contact with eyes and mouth.
2,lf irritation or abnormality occurs, stop using and wash with water
3, Please keep this product out of the reach of children

When using section

1, external use,Avoid contact with eyes and mouth.
2,lf irritation or abnormality occurs, stop using and wash with water
3, Please keep this product out of the reach of children

STOP USE

1, external use, Avoid contact with eyes and mouth.
2,lf irritation or abnormality occurs, stop using and wash with water
3, Please keep this product out of the reach of children

KEEP OUT OF REACH OF CHILDREN

Please keep this product out of the reach of children

INACTIVE INGREDIENT

POTASSIUM ALUM , SODIUM ALGINATE